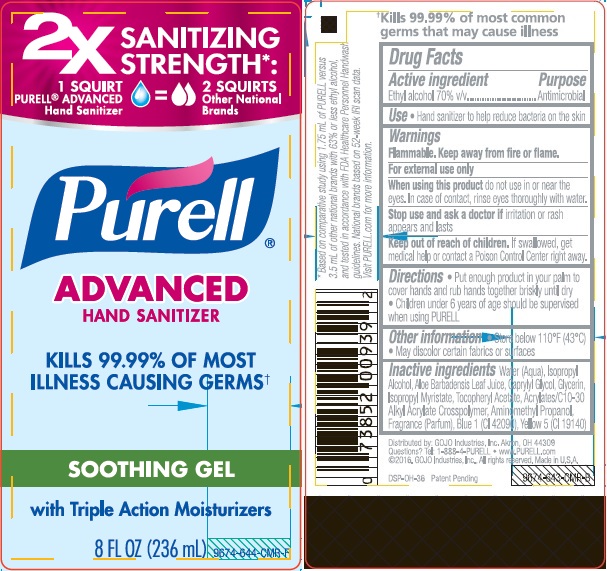 DRUG LABEL: Purell Advanced Soothing
NDC: 21749-713 | Form: GEL
Manufacturer: GOJO Industries, Inc.
Category: otc | Type: HUMAN OTC DRUG LABEL
Date: 20241211

ACTIVE INGREDIENTS: ALCOHOL 0.7 mL/1 mL
INACTIVE INGREDIENTS: WATER; ISOPROPYL ALCOHOL; ALOE VERA LEAF; CAPRYLYL GLYCOL; GLYCERIN; ISOPROPYL MYRISTATE; .ALPHA.-TOCOPHEROL ACETATE, D-; AMINOMETHYLPROPANOL; FD&C BLUE NO. 1; FD&C YELLOW NO. 5

PURELL Advanced Hand Sanitizer Soothing Gel

Active ingredient

Ethyl alcohol 70% v/v

Purpose

Antimicrobial

Uses

- Hand sanitizer to help reduce bacteria on the skin

Warnings

Flammable. Keep away from fire or flame.

For external use only

When using this product do not use in or near the eyes. In case of contact, rinse eyes thoroughly with water.

Stop use and ask a doctor if irritation or rash appears and lasts

Keep Out of Reach of Children. If swallowed, get medical help or contact a Poison Control Center right away.

Directions

- Put enough product in your palm to cover hands and rub hands together briskly until dry
- Children under 6 years of age should be supervised when using PURELL

Inactive ingredients

Water (Aqua), Isopropyl Alcohol, Aloe Barbadensis Leaf Juice, Caprylyl Glycol, Glycerin, Isopropyl Myristate, Tocopheryl Acetate, Acrylates/C10-30 Alkyl Acrylate Crosspolymer, Aminomethyl Propanol, Fragrance (Parfum), Blue 1 (CI 42090), Yellow 5 (CI 19140)

Distributed by: GOJO Industries, Inc. Akron, OH 44309
Questions? Tel: 1-888-4-PURELL ￭ www.PURELL.com
©2011, GOJO Industries, Inc.
All rights reserved. Made in U.S.A.